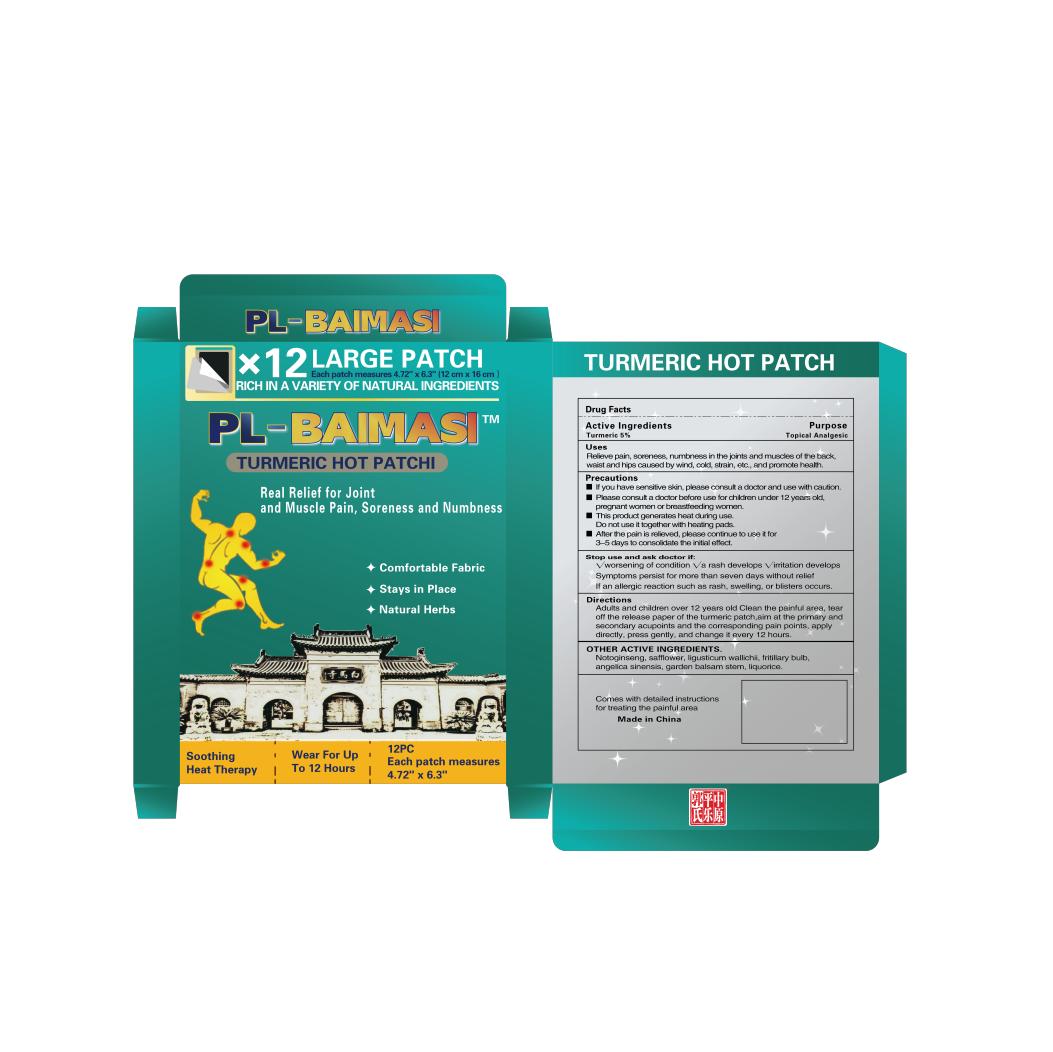 DRUG LABEL: PL-Baimasi
NDC: 85113-001 | Form: PATCH
Manufacturer: Zhengzhou Guoxiaoyi Health Technology Co., Ltd
Category: homeopathic | Type: HUMAN OTC DRUG LABEL
Date: 20250107

ACTIVE INGREDIENTS: TURMERIC 0.05 g/1 g
INACTIVE INGREDIENTS: PANAX NOTOGINSENG TOP; SAFFLOWER; FRITILLARIA CIRRHOSA BULB; ANGELICA BISERRATA WHOLE; ANGELICA SINENSIS ROOT; LIGUSTICUM SINENSE SUBSP. CHUANXIONG ROOT; LICORICE

ACTIVE INGREDIENT

Turmeric

PURPOSE

Helps relieve pain

Keep out of reach of children. If swallowed, seek medical help immediately.

INDICATIONS AND USAGE

1,If you have sensitive skin, please consult a doctor and use with caution.

2,Please consult a doctor before use for children under 12 years old, pregnant women or breastfeeding women.

3,This product generates heat during use. Do not use it together with heating pads.

Stop use and ask doctor if:

1,√worsening of condition √a rash develops √irritation develops

2,Symptoms persist for more than seven days without relief

3,If an allergic reaction such as rash, swelling, or blisters occurs

DOSAGE AND ADMINISTRATION

Stick on the painful area

INACTIVE INGREDIENT

Panax notoginseng,safflower,Chuanxiong,Fritillaria cirrhosa,Chinese angelica,Radix Angelicae Pubescentis,Licorice